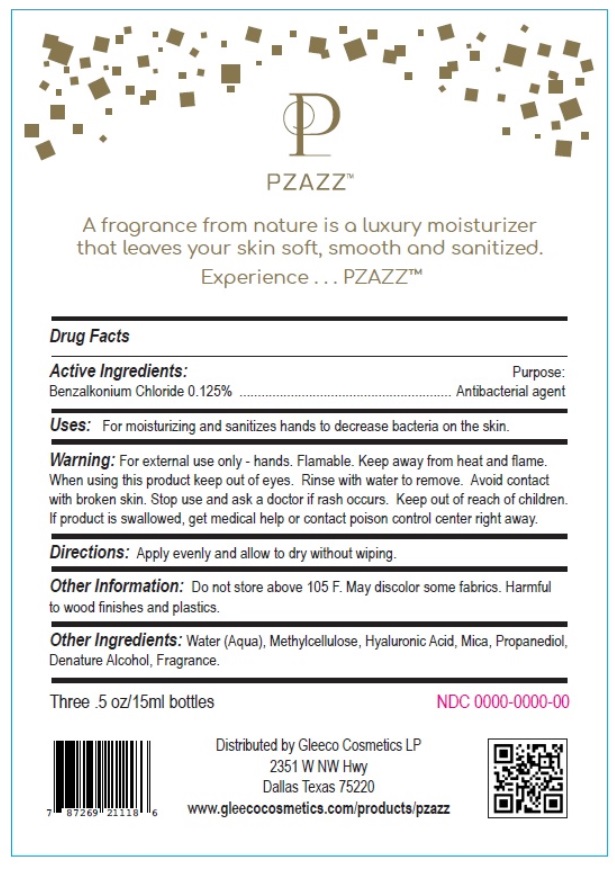 DRUG LABEL: Pzazz
NDC: 82985-001 | Form: GEL
Manufacturer: AXM Premium Cleaning Services, L.P.
Category: otc | Type: HUMAN OTC DRUG LABEL
Date: 20241206

ACTIVE INGREDIENTS: BENZALKONIUM CHLORIDE 0.125 g/100 mL
INACTIVE INGREDIENTS: WATER; HYALURONIC ACID; PROPANEDIOL; MICA; ALCOHOL

Active ingredient

Benzalkonium Chloride 0.125%

Purpose

Antibacterial agent

Uses

For moisturizing and sanitizes hands to decrease bacteria on the skin.

Warning

For external use only hands. Flamable. Keep away from heat and flame.
When using this product keep out of eyes. Rinse with water to remove. Avoid contact with broken skin.

Stop use and ask a doctor if rash occurs. Keep out of reach of children.
If product is swallowed, get medical help or contact poison control center right away.

Direction

Apply evenly and allow to dry without wiping.

Other information

Do not store above 105 F. May discolor some fabrics. Harmful to wood finishes and plastics.

Inactive ingredient

Water (Aqua), Methylcellulose, Hyaluronic Acid, Mica, Propanediol,Denature Alcohol, Fragrance.